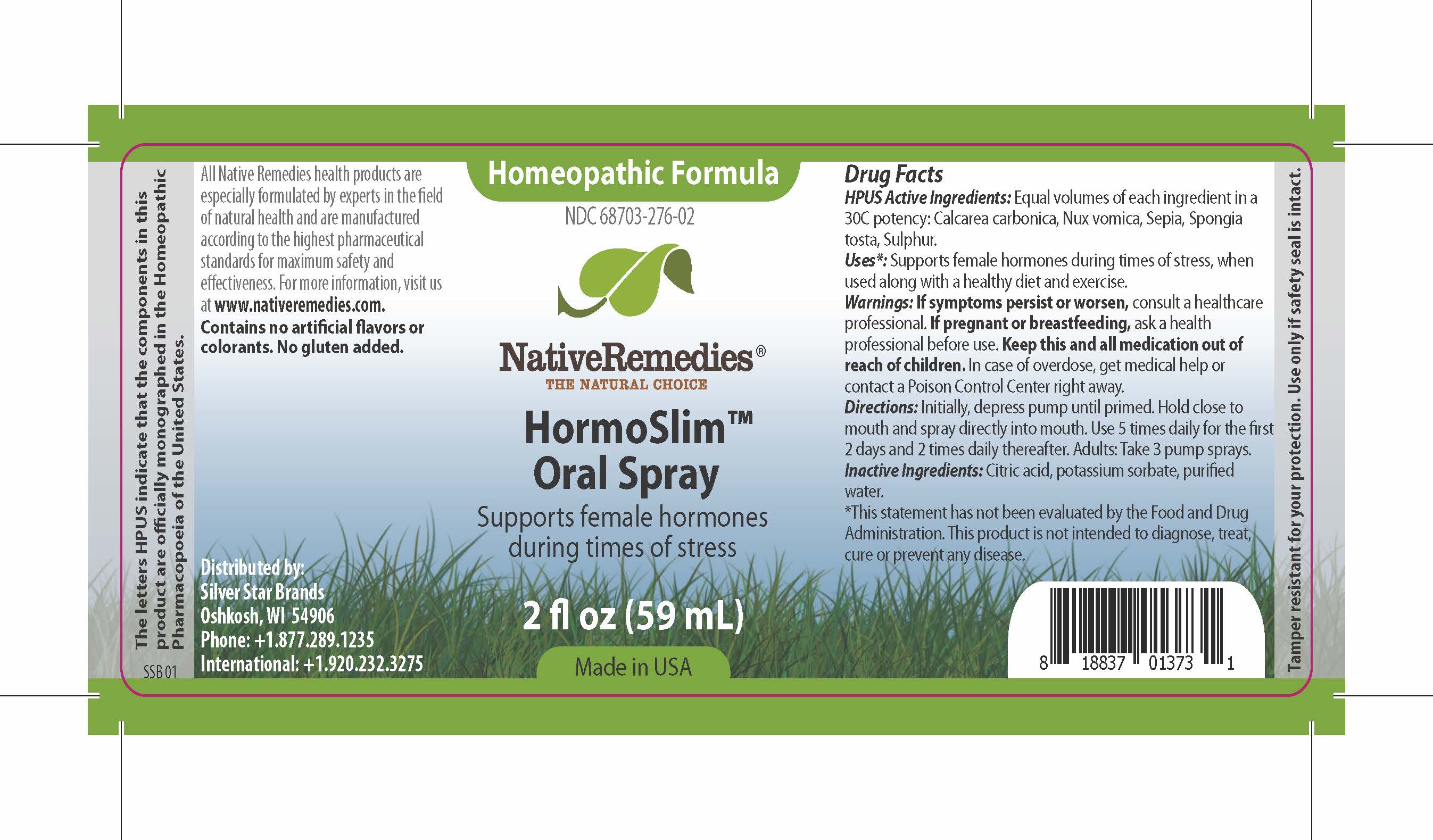 DRUG LABEL: HormoSlim
NDC: 68703-276 | Form: SPRAY
Manufacturer: Silver Star Brands
Category: homeopathic | Type: HUMAN OTC DRUG LABEL
Date: 20170206

ACTIVE INGREDIENTS: CALCIUM CARBONATE 30 [hp_C]/59 mL; SEPIA OFFICINALIS WHOLE 30 [hp_C]/59 mL; SPONGIA OFFICINALIS WHOLE 30 [hp_C]/59 mL; STRYCHNOS NUX-VOMICA WHOLE 30 [hp_C]/59 mL; SULFUR 30 [hp_C]/59 mL
INACTIVE INGREDIENTS: ANHYDROUS CITRIC ACID; POTASSIUM SORBATE; WATER

NativeRemedies® HormoSlim™ Oral Spray

HPUS Active Ingredients:

Equal volumes of each ingredient in a 30C potency: Calcarea carbonica, Nux vomica, Sepia, Spongia tosta, Sulphur.

Uses*:

Supports female hormones during times of stress, when used along with a healthy diet and exercise.

*This statement has not been evaluated by the Food and Drug Administration. This product is not intended to diagnose, treat, cure or prevent any disease.

Warnings:

If symptoms persist or worsen, consult a healthcare professional. If pregnant or breastfeeding, ask a health professional before use. Keep this and all medication out of reach of children. In case of overdose, get medical help or contact a Poison Control Center right away.

Directions:

Initially, depress pump until primed. Hold close to mouth and spray directly into mouth. Use 5 times daily for the first 2 days and 2 times daily thereafter. Adults: Take 3 pump sprays.

OTHER SAFETY INFORMATION

All Native Remedies health products are especially formulated by experts in the field of natural health and are manufactured according to the highest pharmaceutical standards for maximum safety and effectiveness. For more information, visit us at www.nativeremedies.com. Contains no artificial flavors or colorants. No gluten added.

Inactive Ingredients:

Citric acid, potassium sorbate, purified water.

KEEP OUT OF REACH OF CHILDREN

Keep this and all medication out of reach of children. In case of overdose, get medical help or contact a Poison Control Center right away.

PREGNANCY OR BREAST FEEDING

If pregnant or breastfeeding, ask a healthcare professional before use.

PURPOSE

Supports female hormones during times of stress